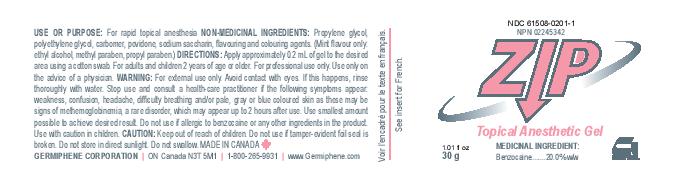 DRUG LABEL: Zip Topical Anesthetic Gel Mint
NDC: 61508-0201 | Form: GEL
Manufacturer: Germiphene Corporation
Category: otc | Type: HUMAN OTC DRUG LABEL
Date: 20170613

ACTIVE INGREDIENTS: BENZOCAINE 20 g/100 g
INACTIVE INGREDIENTS: WATER 0.565 g/100 g; POVIDONE 0.248 g/100 g; ALCOHOL 0.065 g/100 g; D&C YELLOW NO. 10 0.0249 g/100 g; FD&C BLUE NO. 1 0.00155 g/100 g; METHYLPARABEN 0.00016 g/100 g; PROPYLPARABEN 0.00016 g/100 g; SACCHARIN SODIUM 0.697 g/100 g; CARBOMER 934 3.086 g/100 g; PROPYLENE GLYCOL 43.29 g/100 g; POLYETHYLENE GLYCOL 400 30.62 g/100 g

Zip Topical Anesthetic Gel Mint

Use or purpose:

For rapid topical anesthesia

Medicinal ingredient: Benzocaine 20.0% w/w

PURPOSE

Topical Anesthetic Gel

INACTIVE INGREDIENT

Non-Medicinal Ingredients: Propylene glycol, polyethylene glycol, carbomer, povidone, sodium saccharin, flavouring, and colouring agents. (Mint flavour only: ethyl alcohol, methyl paraben, propyl paraben).

DOSAGE AND ADMINISTRATION

Directions: Apply approximately 0.2 mL of gel to the desired area using a cotton swab. For adults and children 2 years of age or older. For professional use only. Use only on the advice of a physician.

WARNINGS

Warning: For external use only. Avoid contact with eyes. If this happens, rinse thoroughly with water. Stop use and consult a health-care practitioner if the following symptoms appear: weakness, confusion, headache, dificulty breathing and/or pale, gray or blue coloured skin as these may be signs of methemoglobinemia, a rare disorder, which may appear up to 2 hours after use. Use smallest amount possible to achieve desired result. Do not use if allergic to benzocaine or any other ingredients in the product. Use with caution in children. Do not use if tamper-evident foil seal is broken. Do not store in direct sunlight. Do not swallow.

Caution: Keep out of reach of children.